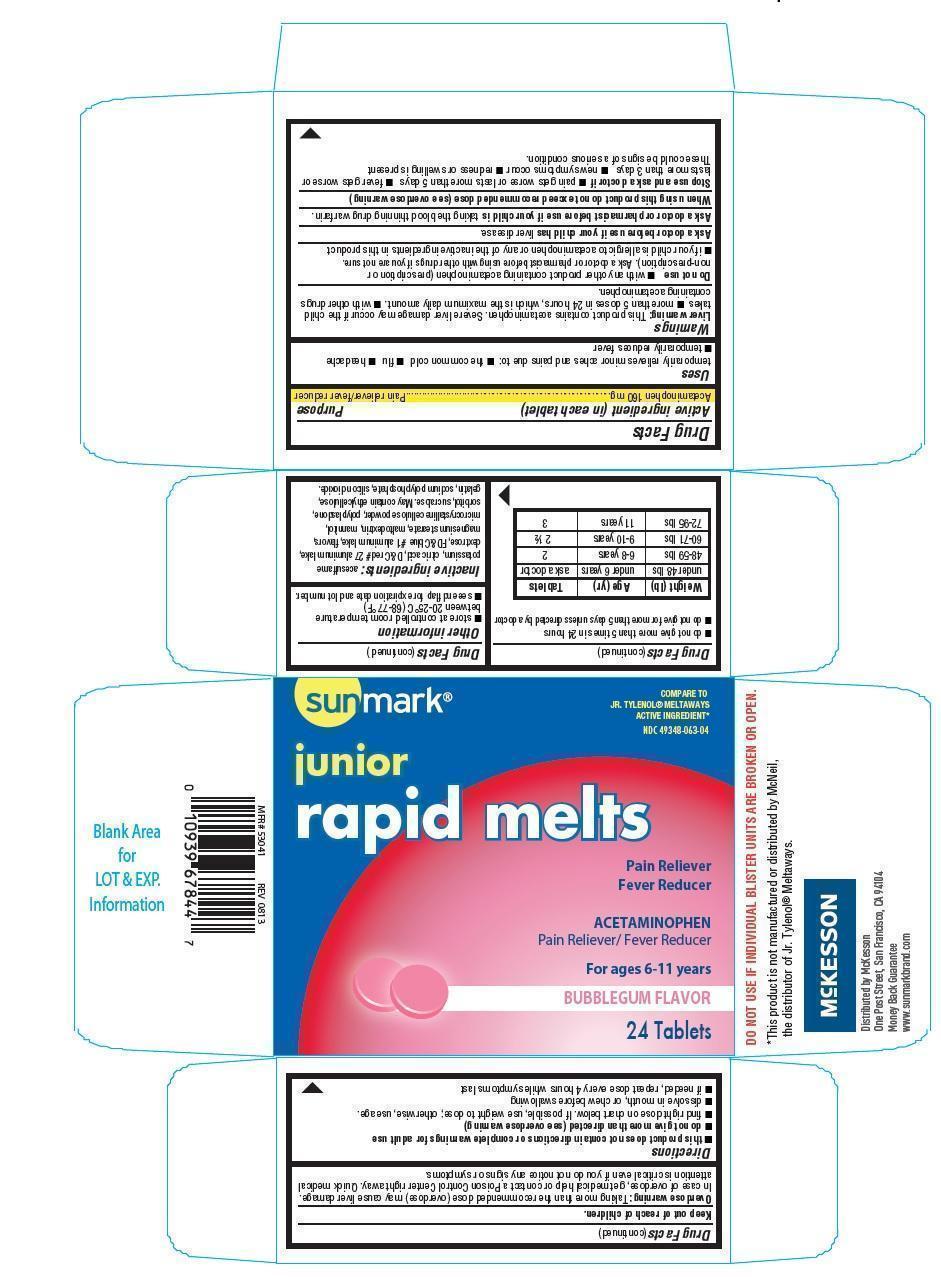 DRUG LABEL: Sunmark Junior Rapid Melts
NDC: 49348-063 | Form: TABLET, CHEWABLE
Manufacturer: Mckesson
Category: otc | Type: HUMAN OTC DRUG LABEL
Date: 20140407

ACTIVE INGREDIENTS: ACETAMINOPHEN 160 mg/1 1
INACTIVE INGREDIENTS: ACESULFAME POTASSIUM; ANHYDROUS CITRIC ACID; D&C RED NO. 27; DEXTROSE; FD&C BLUE NO. 1; MAGNESIUM STEARATE; MALTODEXTRIN; MANNITOL; CELLULOSE, MICROCRYSTALLINE; CROSPOVIDONE; SORBITOL; SUCRALOSE; SILICON DIOXIDE; SODIUM POLYMETAPHOSPHATE

junior rapid melts

Active ingredient (in each tablet)

Acetaminophen 160 mg

Purpose

Pain reliever/ fever reducer

Uses

temporarily relieves minor aches and pains due to:

- the common cold
- flu
- headache
- temporarily reduces fever

Warnings

Liver warning: This product contains acetaminophen. Severe liver damage may occur if the child takes

- more than 5 doses in 24 hours, which is the maximum daily amount.
- with other drugs containing acetaminophen.

Do not use

- with any other product containing acetaminophen (prescription or nonprescription). Ask a doctor or pharmacist before using with other drugs if you are not sure.
- if your child is allergic to acetaminophen or any of the inactive ingredients in this product.

Ask a doctor before use if your child has

liver disease

Ask a doctor or pharmacist before use if your child is

taking the blood thinning drug warfarin

When using this product do not exceed recommended dose (see overdose warning)

Stop use and ask a doctor if

- pain gets worse or lasts more than 5 days
- fever gets worse or lasts more than 3 days
- new symptoms occur
- redness or swelling is present

These could be signs of a serious condition

Keep out of reach of children.

Overdose warning: Thaking more than the recommended dose (overdose) may cause liver damage. In case of overdose, get medical help or contact a poison control center right away. Quick medical attention is critical even if you do not notice any signs or symptoms.

Directions

- this product does not contain directions or complete warnings for adult dose
- do not give more than directed (see overdose warning)
- find right dose on chart below. If possible, use weight to dose; otherwise, use age.
- dissolve in mouth, or chew before swallowing
- if needed, repeat dose every 4 hours while symptoms last
- do not give more than 5 times in 24 hours
- do not give more than 5 days unless directed by a doctor.

Weight (lb) | Age (yr) | Tablets
under 48 lbs | under 6 years | ask a doctor
48-59 lbs | 6-8 years | 2
60-71 lbs | 9-10 years | 2 1/2
72-95 lbs | 11 years | 3

Other information

- store at controlled room temperature betweeen 20-25oC(68-77oF)
- see end flap for expiration date and lot number

Inactive ingredients

acesulfame pottasium, citric acid, D&C red 27 aluminum lake, dextrose, FD&C blue 1 aluminum lake, flavors, magnesium stearate, maltodextrin, mannitol, microcrystalline cellulose powder, polyplasdone, sorbitol, sucralose.

May contain ethylcellulose, gelatin, sodium polyphosphate, silicon dioxide.

PDP

Sunmark

Junior Rapid Melts

Compare to JR. Tylenol Meltaways active ingredient

Pain reliever

Fever reducer

Acetaminophen

Pain reliever/Fever Reducer

For ages 6-11 years

Bubblegum Flavor

24 Tablets